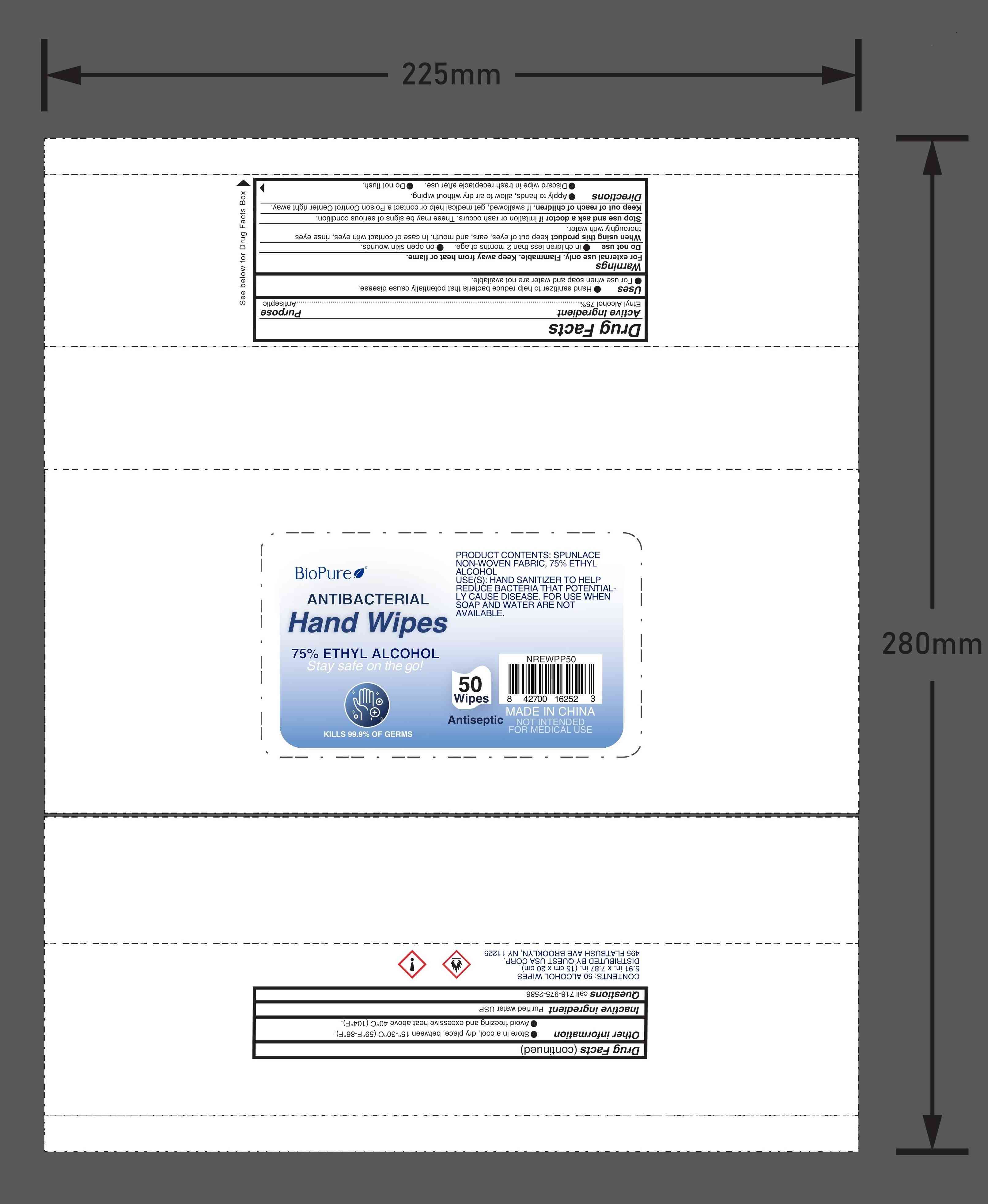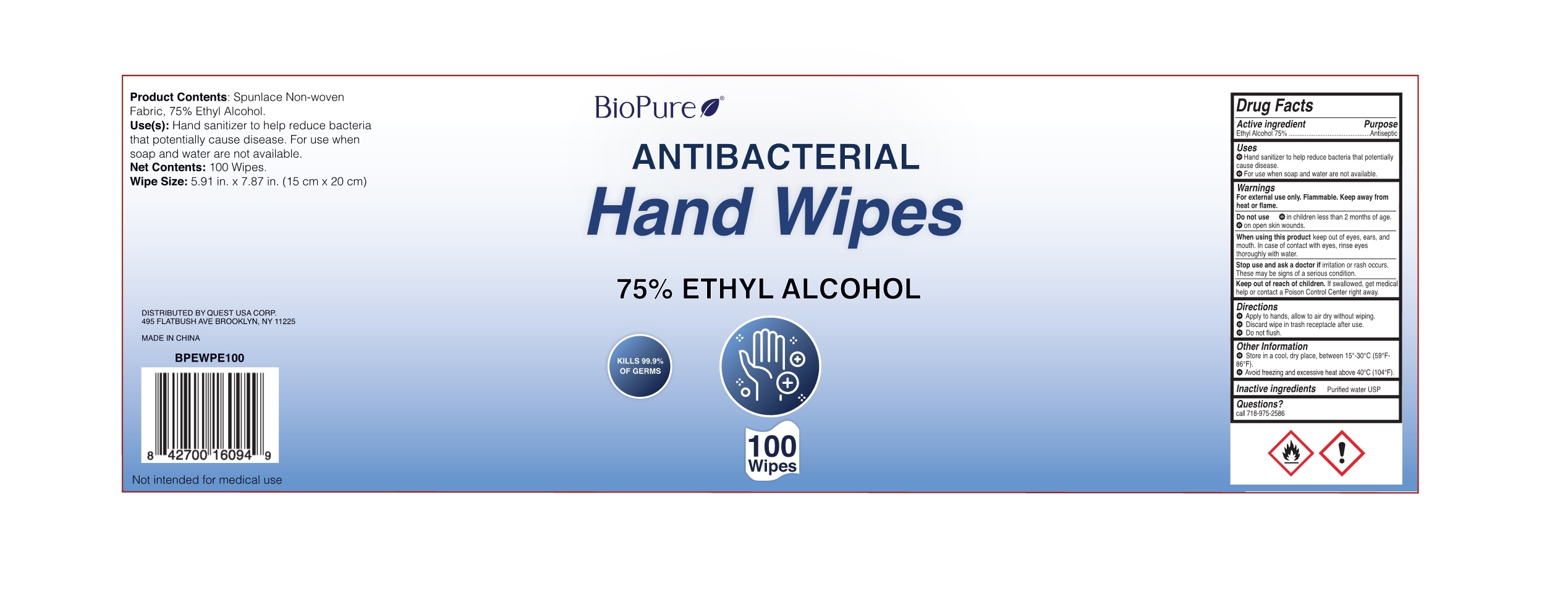 DRUG LABEL: Antibacterial Hand Wipes
NDC: 79866-003 | Form: CLOTH
Manufacturer: Osike Cosmetics Co., Ltd.
Category: otc | Type: HUMAN OTC DRUG LABEL
Date: 20220120

ACTIVE INGREDIENTS: ALCOHOL 75 mL/100 1
INACTIVE INGREDIENTS: WATER

79866-003
Antibacterial Hand Wipes

Active Ingredient(s)

Ethyl Alcohol 75%

Purpose

Antiseptic

Use

● Hand sanitizer to help reduce bacteria that potentially cause disease.
●For use when soap and water are not available

Warnings

For external use only. Flammable. keep away from fire or flame.

Do not use

●in children less than 2 months of age.
●on open skin wounds.

When using this product keep out of eyes, ears, and mouth. In case of contact with eyes, rinse eyes thoroughly with water

Stop use and ask a doctor if irritation or rash occurs. These may be signs of serious condition.

Keep out of reach of children. If swallowed. get medical help or contact a Poison Control Center right away.

Directions

● Apply to hands, allow to air dry without wiping .
●Discard wipe in trash receptacle after use.
●Do not flush

Other information

●Store in a cool, dry place, between 15°-30°C（59°F-86°F）
●Avoid Freezing and excessive heat above 40°C（104 °F）

Inactive ingredients

Purified water USP